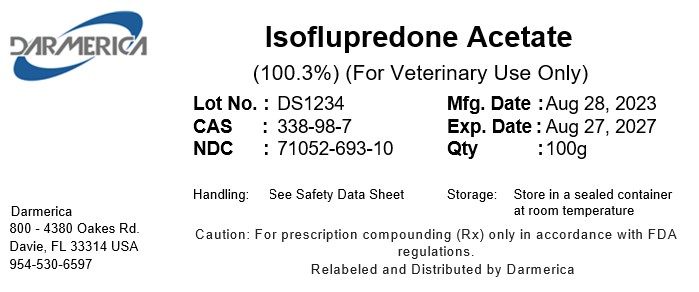 DRUG LABEL: Isoflupredone Acetate
NDC: 71052-693 | Form: POWDER
Manufacturer: DARMERICA, LLC
Category: other | Type: BULK INGREDIENT - ANIMAL DRUG
Date: 20251015

ACTIVE INGREDIENTS: ISOFLUPREDONE ACETATE 1 kg/1 kg

Isoflupredone Acetate